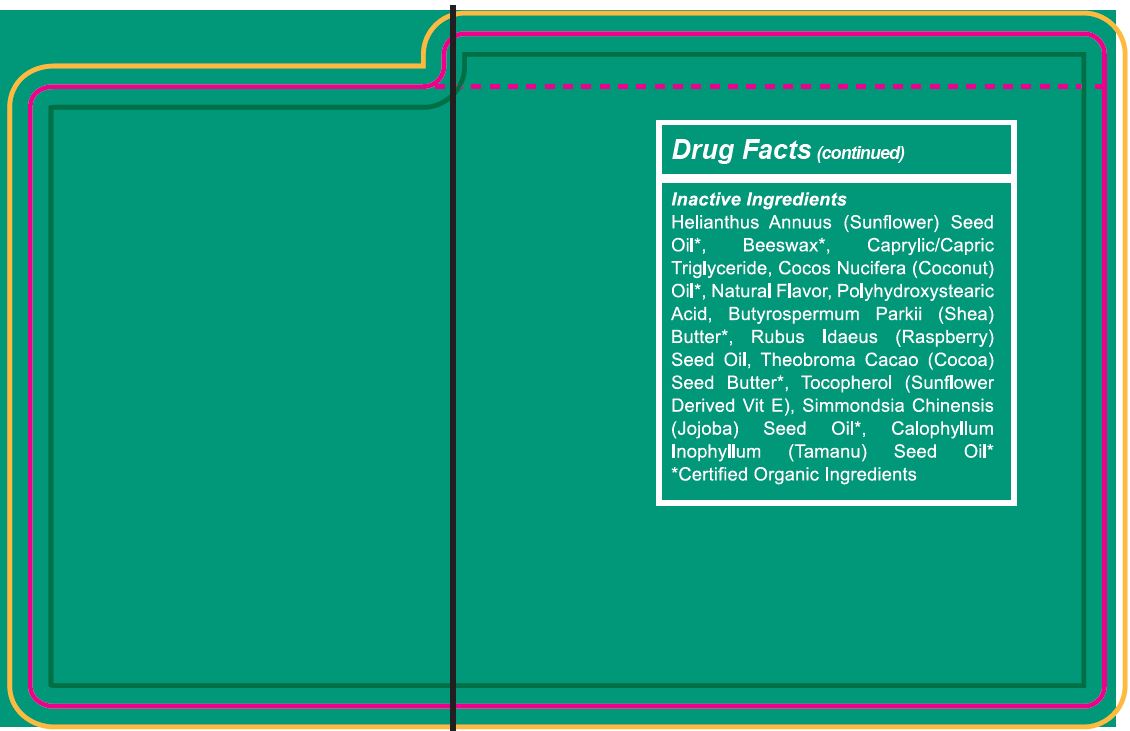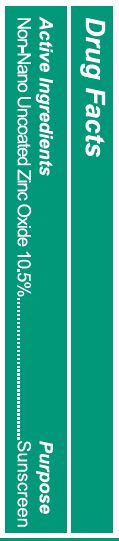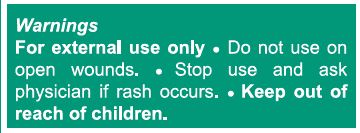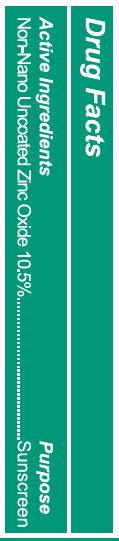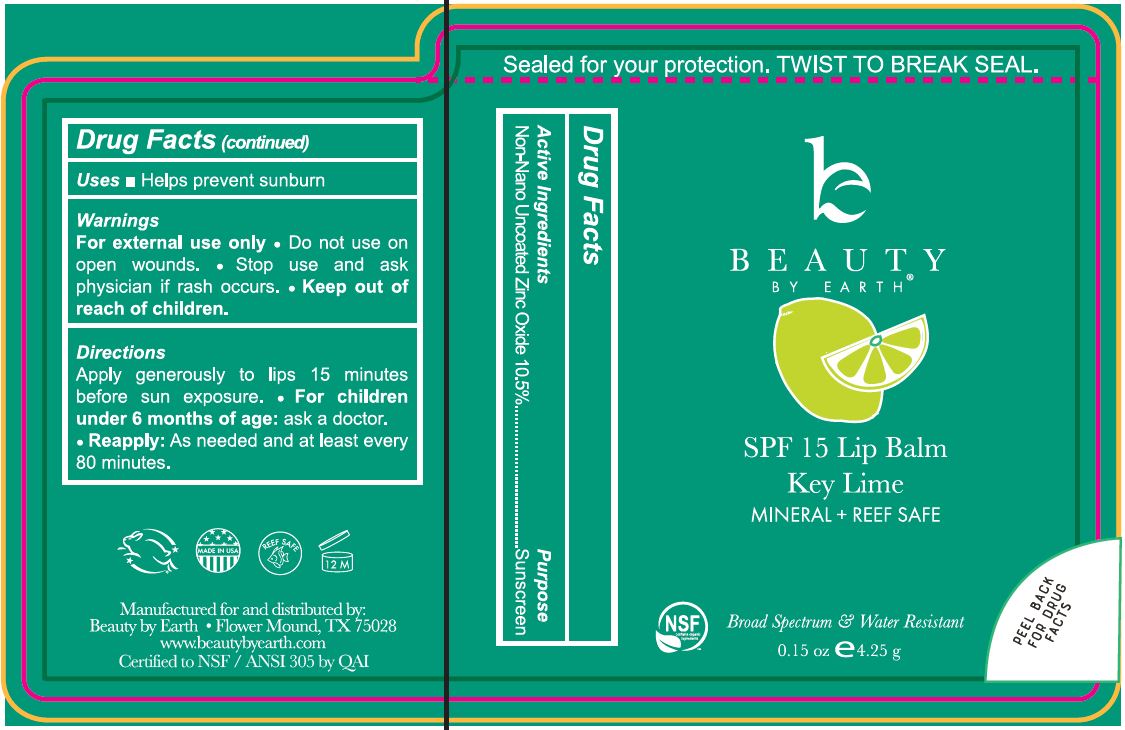 DRUG LABEL: SPF 15 Lip Balm Key Lime
NDC: 62932-225 | Form: STICK
Manufacturer: Private Label Select Ltd CO
Category: otc | Type: HUMAN OTC DRUG LABEL
Date: 20201228

ACTIVE INGREDIENTS: ZINC OXIDE 10 g/100 g
INACTIVE INGREDIENTS: SUNFLOWER OIL; SHEA BUTTER; .DELTA.-TOCOPHEROL; WHITE WAX; MEDIUM-CHAIN TRIGLYCERIDES; COCONUT OIL; RASPBERRY SEED OIL; COCOA BUTTER; .ALPHA.-TOCOPHEROL, D-; .BETA.-TOCOPHEROL; JOJOBA OIL; TAMANU OIL; POLYHYDROXYSTEARIC ACID (2300 MW); .GAMMA.-TOCOPHEROL; POLYHYDROXYSTEARIC ACID STEARATE

Beauty By Earth SPF 15 Lip Balm Key Lime